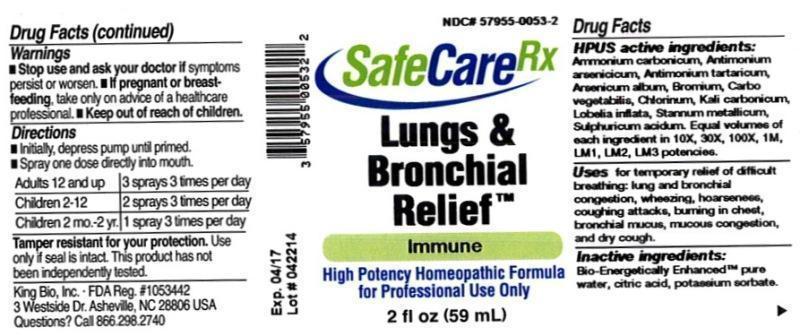 DRUG LABEL: Lungs and Bronchial Relief
NDC: 57955-0053 | Form: LIQUID
Manufacturer: King Bio Inc.
Category: homeopathic | Type: HUMAN OTC DRUG LABEL
Date: 20140505

ACTIVE INGREDIENTS: AMMONIUM CARBONATE 10 [hp_X]/59 mL; ANTIMONY ARSENATE 10 [hp_X]/59 mL; ANTIMONY POTASSIUM TARTRATE 10 [hp_X]/59 mL; ARSENIC TRIOXIDE 10 [hp_X]/59 mL; BROMINE 10 [hp_X]/59 mL; ACTIVATED CHARCOAL 10 [hp_X]/59 mL; CHLORINE 10 [hp_X]/59 mL; POTASSIUM CARBONATE 10 [hp_X]/59 mL; LOBELIA INFLATA 10 [hp_X]/59 mL; TIN 10 [hp_X]/59 mL; SULFURIC ACID 10 [hp_X]/59 mL
INACTIVE INGREDIENTS: CITRIC ACID MONOHYDRATE; POTASSIUM SORBATE; WATER

Lungs and Bronchial Relief™

ACTIVE INGREDIENT

Drug Facts__________________________________________________________________________________________________________

HPUS active ingredients: Ammonium carbonicum, Antimonium arsenicicum, Antimonium tartaricum, Arsenicum album, Bromium, Carbo vegetabilis, Chlorinum, Kali carbonicum, Lobelia inflata, Stannum metallicum, Sulphuricum acidum. Equal volumes of each ingredient in 10X, 30X, 100X, 1M, LM1, LM2, LM3 potencies.

INDICATIONS AND USAGE

Uses for temporary relief of difficult breathing: lung and bronchial congestion, wheezing, hoarseness, coughing attacks, burning in chest, bronchial mucus, mucous congestion, and dry cough

Inactive Ingredients:

Bio-Energetically Enhanced™ pure water, citric acid and potassium sorbate.

Warnings

- Stop use and ask your doctor if symptoms persist or worsen.
- If pregnant or breast-feeding, take only on advice of a healthcare professional.

- Keep out of reach of children.

Directions

- Initially, depress pump until primed.
- Spray one dose directly into mouth.
- Adults 12 and up: 3 sprays 3 times per day.
- Children 2-12: 2 sprays 3 times per day.
- Children 2 mo.2 yr 1 spray 3 times per day.

OTHER SAFETY INFORMATION

Tamper resistant for your protection. Use only if seal is intact.

PURPOSE

Uses for temporary relief of difficult breathing:

- lung and bronchial congestion
- wheezing
- hoarseness
- couthing attacks
- burning in chest
- bronchial mucus
- mucous congestion
- dry cough